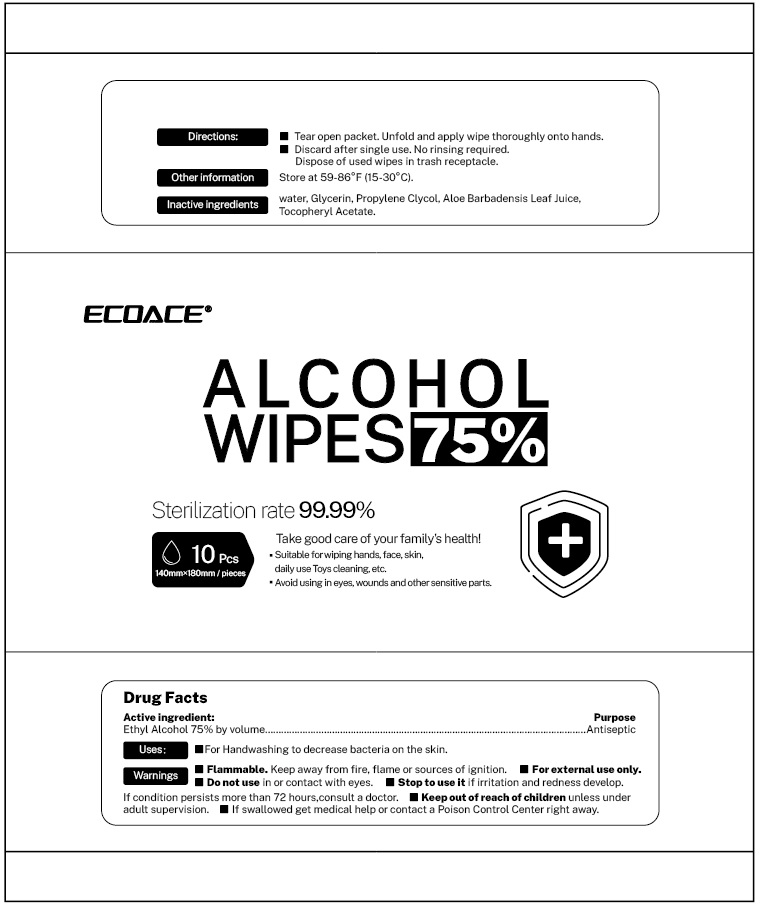 DRUG LABEL: Disinfectant Wet Tissues
NDC: 78352-101 | Form: CLOTH
Manufacturer: Blue Sky Digital Technology Co., Ltd.
Category: otc | Type: HUMAN OTC DRUG LABEL
Date: 20200522

ACTIVE INGREDIENTS: ALCOHOL 1 mL/1 1
INACTIVE INGREDIENTS: HYDROGEN PEROXIDE; GLYCERIN; PROPYLENE GLYCOL; WATER

Disinfectant Wet Tissues

Disinfectant Wet Tissues

Active Ingredient(s)

Alcohol 1mL/pcs. Purpose: Antiseptic

Purpose

Antiseptic, Disinfectant Wet Tissues

Use

For Handwashing to decrease bacteria on the skin.

Warnings

For external use only. Flammable. Keep away from heat or flame

Do not use

- in children less than 2 months of age
- on open skin wounds

When using this product keep out of eyes, ears, and mouth. In case of contact with eyes, rinse eyes thoroughly with water.
Stop use and ask a doctor if irritation or rash occurs. These may be signs of a serious condition.
Keep out of reach of children. If swallowed, get medical help or contact a Poison Control Center right away.

Stop use and ask a doctor if irritation or rash occurs. These may be signs of a serious condition.

Keep out of reach of children. If swallowed, get medical help or contact a Poison Control Center right away.

Directions

- Tear open packet. Unfold and apply wipe thoroughly onto hands.
- Discard after single use. No rinsing reqiured.
- Dispose of uesd wipes in trash receptacle.
- Supervise children under 6 years of age when using this product to avoid swallowing.

Other information

- Store between 15-30C (59-86F)
- Avoid freezing and excessive heat above 40C (104F)

Inactive ingredients

WATER
Propylene Glycol
HYDROGEN PEROXIDE
GLYCERIN